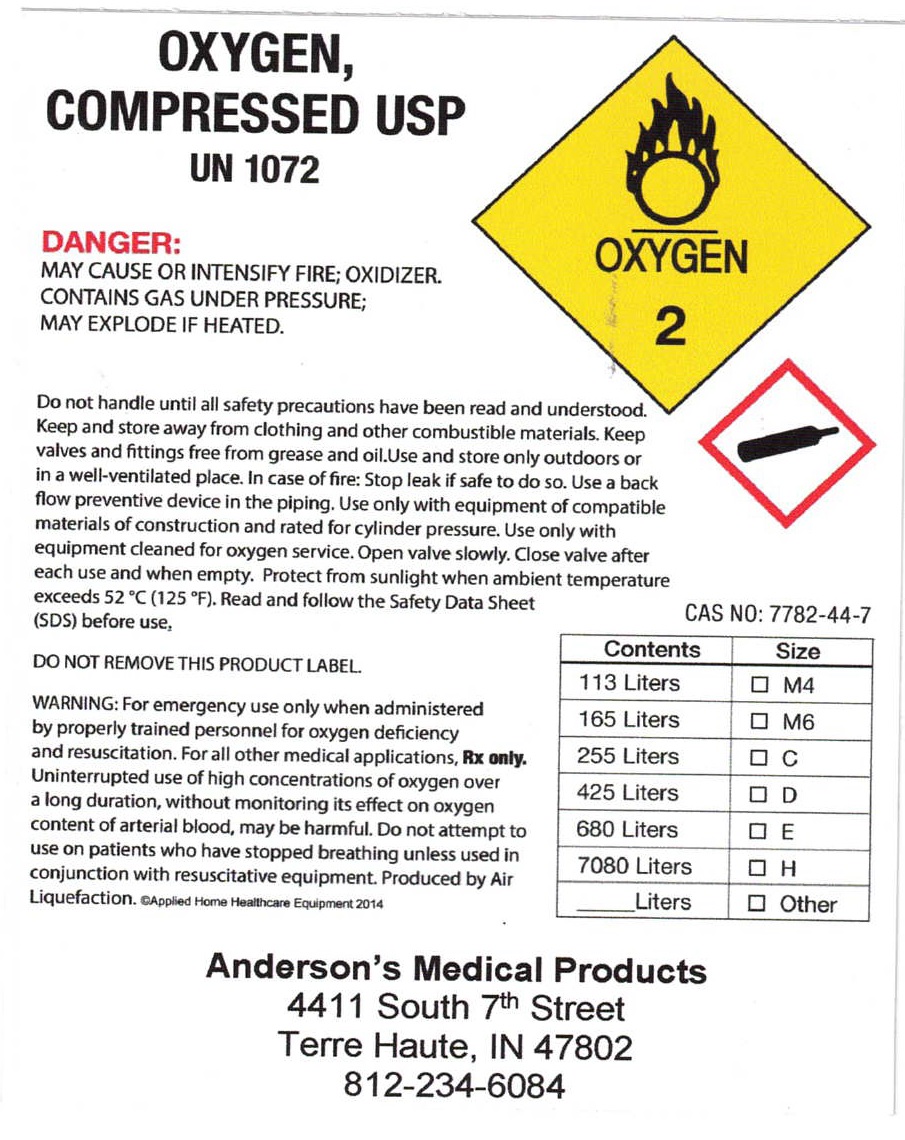 DRUG LABEL: OXYGEN
NDC: 55128-111 | Form: GAS
Manufacturer: Terre Haute Home Health Care Products dba Anderson's Medical Products
Category: prescription | Type: HUMAN PRESCRIPTION DRUG LABEL
Date: 20251023

ACTIVE INGREDIENTS: OXYGEN 99 L/100 L

OXYGEN COMPRESSED USP

res